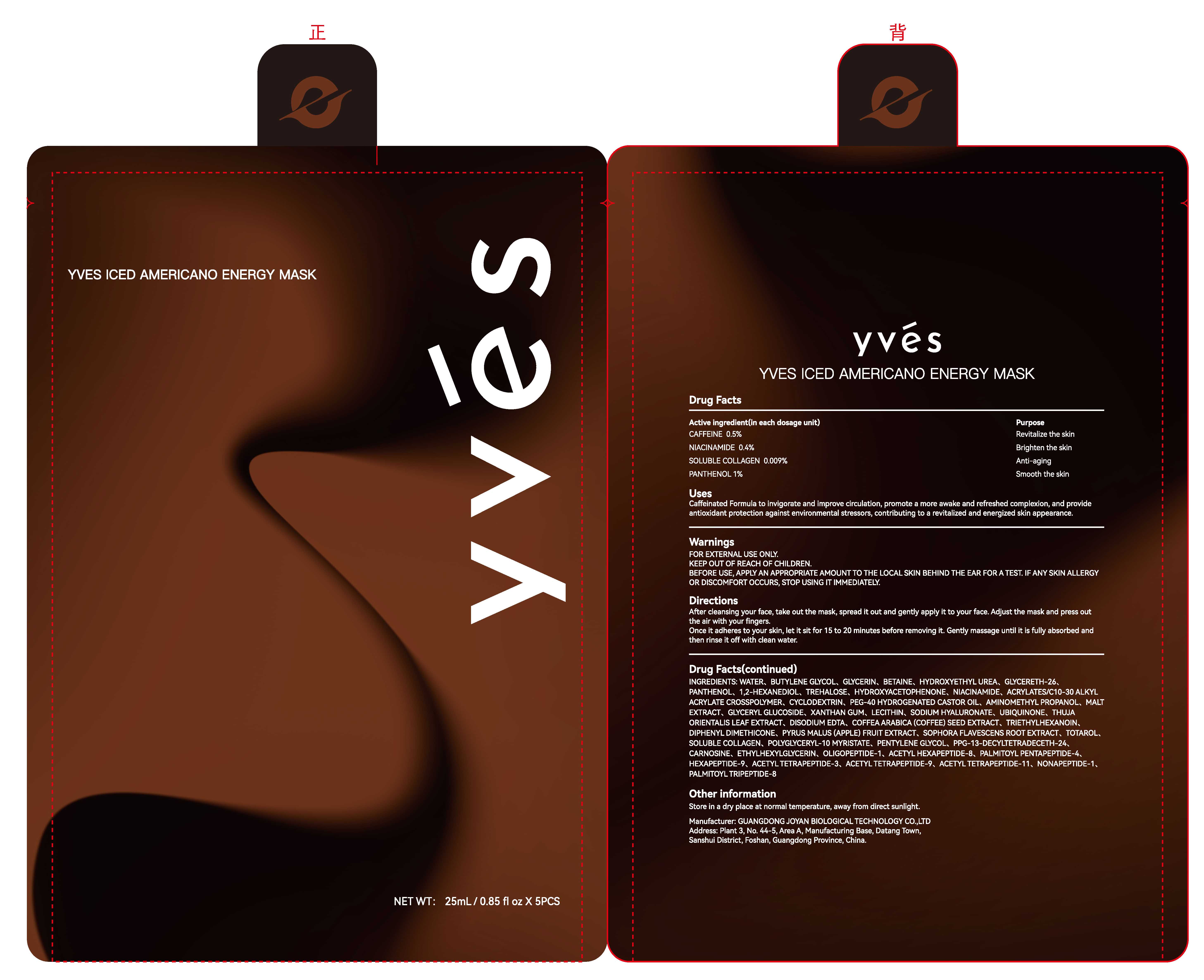 DRUG LABEL: YVES ICED AMERICANO ENERGY MASK
NDC: 85779-001 | Form: LIQUID
Manufacturer: Guangdong Joyan Biological Technology Co.,Ltd
Category: otc | Type: HUMAN OTC DRUG LABEL
Date: 20250610

ACTIVE INGREDIENTS: PANTHENOL 1 g/100 mL; CAFFEINE 0.5 g/100 mL; NIACINAMIDE 0.4 g/100 mL; COLLAGEN ALPHA-1(VII) CHAIN 0.009 g/100 mL
INACTIVE INGREDIENTS: WATER; BUTYLENE GLYCOL; HYDROXYETHYL UREA

85779-001 YVES ICED AMERICANO ENERGY MASK

ACTIVE INGREDIENT

CAFFEINE 0.5%
NIACINAMIDE 0.4%
SOLUBLE COLLAGEN 0.009%
PANTHENOL 1%

PURPOSE

Revitalize the skin
Brighten the skin

Anti-aging

Smooth the skin

KEEP OUT OF REACH OF CHILDREN.

INDICATIONS AND USAGE

Caffeinated Formula to invigorate and improve circulation, promotemore awake and refreshed complexion, and provideantioxidant protection against environmental stressors, contributing to a revitalized and energized skin appearance.

WARNINGS

FOR EXTERNAL USE ONLY.

WHEN USING

BEFORE USE, APPLY AN APPROPRIATE AMOUNT TO THE LOCAL SKIN BEHIND THE EAR FOR A TEST. IF ANY SKIN ALLERGYOR DISCOMFORT OCCURS, STOP USING IT IMMEDIATELY.

Directions
After cleansing your face, ake out the mask, spread it out and gently apply it to your face. Adjust the mask and press outthe air with your fingers.
Once it adheres to your skin, let it sit for 15 to 20 minutes before removing it. Gently massage until it is fully absorbed andthen rinse it off with clean water.

INACTIVE INGREDIENT

WATER
BUTYLENE GLYCOL
HYDROXYETHYL UREA